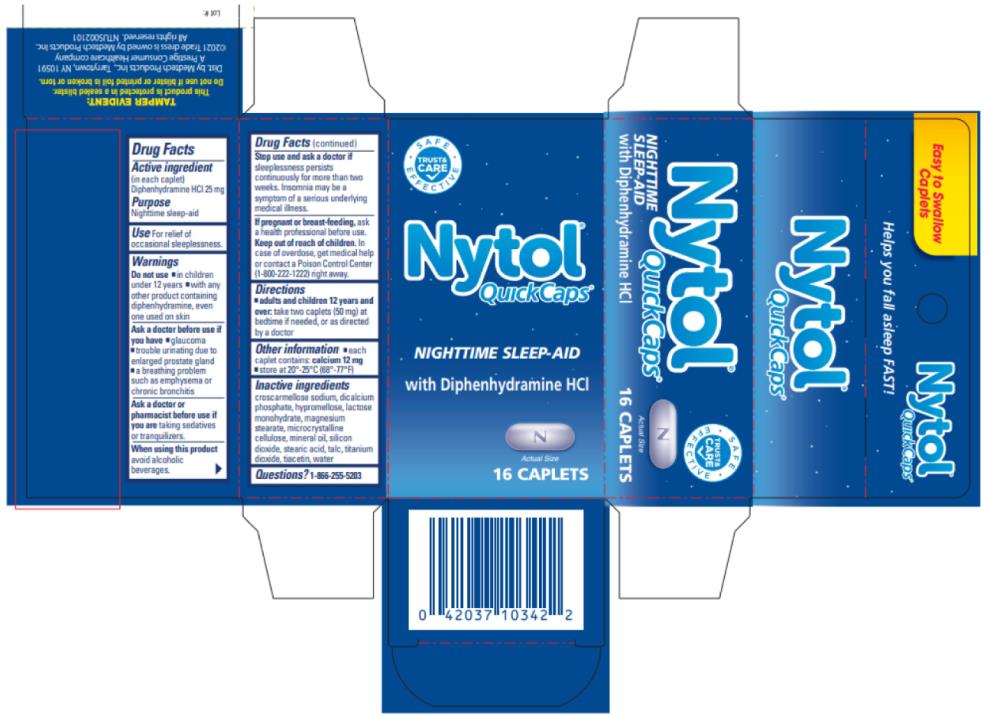 DRUG LABEL: Nytol
NDC: 63029-211 | Form: TABLET
Manufacturer: Medtech Products Inc.
Category: otc | Type: HUMAN OTC DRUG LABEL
Date: 20241025

ACTIVE INGREDIENTS: DIPHENHYDRAMINE HYDROCHLORIDE 25 mg/1 1
INACTIVE INGREDIENTS: CROSCARMELLOSE SODIUM; CALCIUM PHOSPHATE, DIBASIC, ANHYDROUS; HYPROMELLOSE, UNSPECIFIED; LACTOSE, UNSPECIFIED FORM; MAGNESIUM STEARATE; CELLULOSE, MICROCRYSTALLINE; MINERAL OIL; SILICON DIOXIDE; STEARIC ACID; TALC; TITANIUM DIOXIDE; TRIACETIN; WATER

Nytol

Drug Facts

Active ingredient

(in each caplet)

Diphenhydramine HCI 25 mg

Purpose

Nighttime sleep-aid

Use

For relief of occasional sleeplessness.

Warnings

Do not use

- in children over 12 years of age
- with any other product containing diphenhydramine, even one used on skin

Ask a doctor before use if you have

- glaucoma
- trouble urinating due to an enlarged prostate gland

a breathing problem such as emphysema or chronic bronchitis

Ask a doctor or pharmacist before use if you are

taking sedatives or tranquilizers

When using this product

- avoid alcoholic beverages.

Stop use and ask a doctor if

sleeplessness persists continuously for more than 2 weeks. Insomnia may be a symptom of serious underlying medical illness.

If pregnant or breast-feeding,

ask a health care professional before use.

Keep out of reach of children.

In case of overdose, get medical help or contact a Poison Control Center (1-800-222-1222) right away.

Directions

- adults and children 12 years of age and over: take 2 caplets (50 mg) at bedtime if needed, or as directed by a doctor

Other information

- each caplet contains: calcium 12 mg
- store below 25ºC (77ºF)

Inactive ingredients

croscarmellose sodium, dicalcium phosphate, hypromellose, lactose monohydrate, magnesium stearate, microcrystalline cellulose, mineral oil, silicon dioxide, stearic acid, talc, titanium dioxide, triacetin, water

Questions?

1-866-255-5203

TAMPER EVIDENT FEATURE:

This product is protected in a sealed blister. Do not use if blister or printed foil is broken or torn.

PRINCIPAL DISPLAY PANEL

Nytol® QUICKCAPS®
with Diphenhydramine HCl
NIGHTTIME SLEEP-AID
THIS PACKAGE FOR HOUSEHOLDS WITHOUT YOUNG CHILDREN
16 CAPLETS